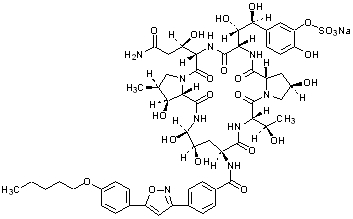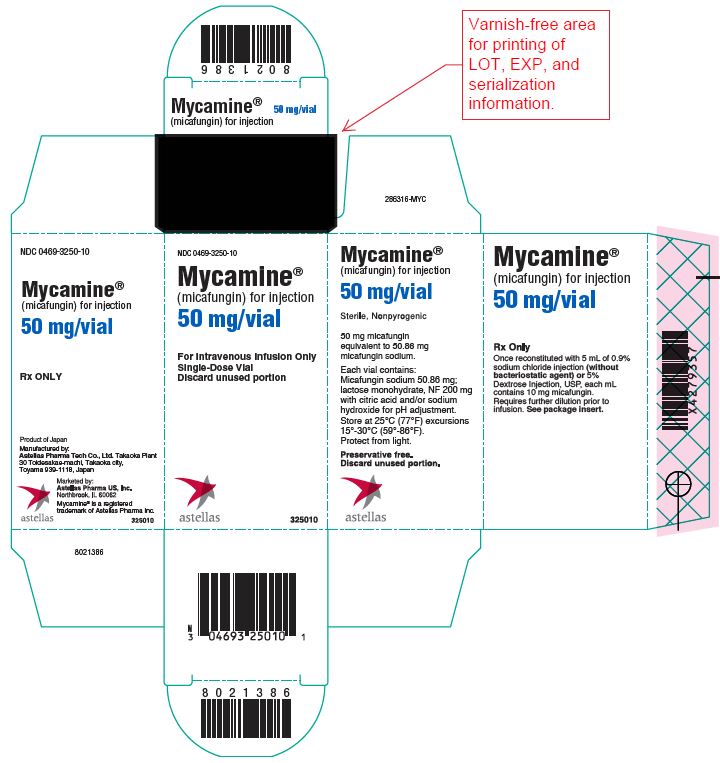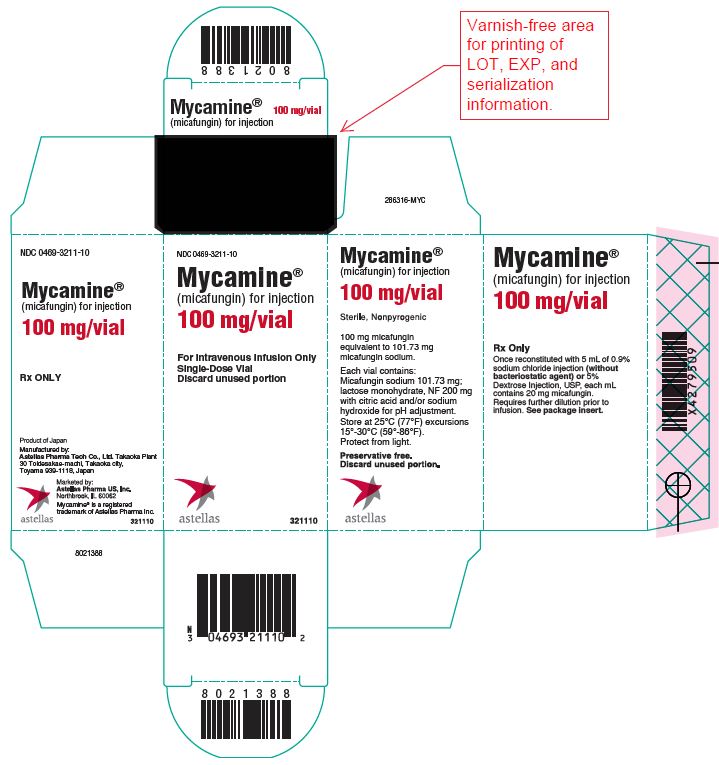 DRUG LABEL: Mycamine
NDC: 0469-3250 | Form: INJECTION, POWDER, LYOPHILIZED, FOR SOLUTION
Manufacturer: Astellas Pharma US, Inc.
Category: prescription | Type: HUMAN PRESCRIPTION DRUG LABEL
Date: 20241227

ACTIVE INGREDIENTS: MICAFUNGIN SODIUM 10 mg/1 mL
INACTIVE INGREDIENTS: ANHYDROUS CITRIC ACID; LACTOSE MONOHYDRATE; SODIUM HYDROXIDE

HIGHLIGHTS OF PRESCRIBING INFORMATION

These highlights do not include all the information needed to use MYCAMINE® safely and effectively. See full prescribing information for MYCAMINE®.
MYCAMINE® (micafungin for injection), for intravenous use
Initial U.S. Approval: 2005

RECENT MAJOR CHANGES

Indications and Usage (1) 12/2019
Dosage and Administration, Dosage for Pediatric Patients Younger
than 4 Months of Age (2.3) 12/2019
Warnings and Precautions, Infusion and Injection Site Reactions
(5.5) 12/2019

1 INDICATIONS AND USAGE

MYCAMINE® is an echinocandin indicated in adult and pediatric patients for (1):

- Treatment of Candidemia, Acute Disseminated Candidiasis, Candida Peritonitis and Abscesses in adult and pediatric patients 4 months of age and older.
- Treatment of Candidemia, Acute Disseminated Candidiasis, Candida Peritonitis and Abscesses without meningoencephalitis and/or ocular dissemination in pediatric patients younger than 4 months of age.
- Treatment of Esophageal Candidiasis in adult and pediatric patients 4 months of age and older.
- Prophylaxis of Candida Infections in adult and pediatric patients 4 months of age and older undergoing Hematopoietic Stem Cell Transplantation (HSCT).

Limitations of Use

- The safety and effectiveness of MYCAMINE have not been established for the treatment of candidemia with meningoencephalitis and/or ocular dissemination in pediatric patients younger than 4 months of age as a higher dose may be needed. (1, 2.3, 8.4)
- MYCAMINE has not been adequately studied in patients with endocarditis, osteomyelitis or meningoencephalitis due to Candida. (1)
- The efficacy of MYCAMINE against infections caused by fungi other than Candida has not been established. (1)

2 DOSAGE AND ADMINISTRATION

Recommended Dosage Administered by Indication, Weight and Age (2.1, 2.2, 2.3, 8.4)

Adult | Pediatric Patients; 4 Months and Older 30 kg or less | Pediatric Patients; 4 Months and Older greater than 30 kg | Pediatric Patients Younger than 4 Months of Age
Treatment of Candidemia, Acute Disseminated Candidiasis, Candida Peritonitis and Abscesses
100 mg daily | 2 mg/kg/day (maximum 100 mg daily) |  | See below
Treatment of Candidemia, Acute Disseminated Candidiasis, Candida Peritonitis and Abscesses without Meningoencephalitis and/or Ocular Dissemination
See above | See above |  | 4 mg/kg/day
Treatment of Esophageal Candidiasis
150 mg daily | 3 mg/kg/day | 2.5 mg/kg/day (maximum 150 mg daily) | Not approved
Prophylaxis of Candida Infections in HSCT Recipients
50 mg daily | 1 mg/kg/day (maximum 50 mg daily) |  | Not approved

- Infuse over 1 hour. (2.5)
- See Full Prescribing Information for intravenous (IV) preparation and administration instructions. (2)

3 DOSAGE FORMS AND STRENGTHS

- For injection: 50 mg single-dose vial. (3)
- For injection: 100 mg single-dose vial. (3)

4 CONTRAINDICATIONS

MYCAMINE is contraindicated in persons with known hypersensitivity to micafungin sodium, any component of MYCAMINE, or other echinocandins. (4)

5 WARNINGS AND PRECAUTIONS

- Hypersensitivity Reactions: Anaphylaxis and anaphylactoid reactions (including shock) have been observed. Discontinue MYCAMINE and administer appropriate treatment. (5.1)
- Hematological Effects: Isolated cases of acute intravascular hemolysis, hemolytic anemia and hemoglobinuria have been reported. Monitor rate of hemolysis. Discontinue if severe. (5.2)
- Hepatic Effects: Abnormalities in liver tests; isolated cases of hepatic impairment, hepatitis, and hepatic failure have been observed. Monitor hepatic function. Discontinue if severe dysfunction occurs. (5.3)
- Renal Effects: Elevations in BUN and creatinine; isolated cases of renal impairment or acute renal failure have been reported. Monitor renal function. (5.4)
- Infusion and Injection Site Reactions can occur including rash, pruritus, facial swelling, and vasodilatation. Monitor infusion closely, slow infusion rate if necessary. (2.5, 5.5)

6 ADVERSE REACTIONS

- Most common adverse reactions across adult and pediatric clinical trials for all indications include diarrhea, nausea, vomiting, abdominal pain, pyrexia, thrombocytopenia, neutropenia, and headache. (6.1)
- In pediatric patients younger than 4 months of age, the following additional common adverse reactions were reported at an incidence rate of ≥15%: sepsis, acidosis, anemia, oxygen saturation decreased and hypokalemia. (6.1)

To report SUSPECTED ADVERSE REACTIONS, contact Astellas Pharma US, Inc. at 1-800-727-7003 or FDA at 1-800-FDA-1088 or www.fda.gov/medwatch.

7 DRUG INTERACTIONS

Monitor for sirolimus, itraconazole or nifedipine toxicity, and dosage of sirolimus, itraconazole or nifedipine should be reduced, if necessary. (7)

8 USE IN SPECIFIC POPULATIONS

Pregnancy – Based on animal data, MYCAMINE may cause fetal harm. Advise pregnant women of the risk to the fetus. (8.1)

FULL PRESCRIBING INFORMATION

1 INDICATIONS AND USAGE

MYCAMINE® is indicated for:

• Treatment of Candidemia, Acute Disseminated Candidiasis, Candida Peritonitis and Abscesses in adult and pediatric patients 4 months of age and older [see Clinical Studies (14.1) and Use in Specific Populations (8.4)].
• Treatment of Candidemia, Acute Disseminated Candidiasis, Candida Peritonitis and Abscesses without meningoencephalitis and/or ocular dissemination in pediatric patients younger than 4 months of age [see Use in Specific Populations (8.4)].
• Treatment of Esophageal Candidiasis in adult and pediatric patients 4 months of age and older [see Clinical Studies (14.2)].
• Prophylaxis of Candida Infections in adult and pediatric patients 4 months of age and older undergoing hematopoietic stem cell transplantation [see Clinical Studies (14.3)].

Limitations of Use

• The safety and effectiveness of MYCAMINE have not been established for the treatment of candidemia with meningoencephalitis and/or ocular dissemination in pediatric patients younger than 4 months of age as a higher dose may be needed [see Use in Specific Populations (8.4)].
• MYCAMINE has not been adequately studied in patients with endocarditis, osteomyelitis and meningoencephalitis due to Candida.
• The efficacy of MYCAMINE against infections caused by fungi other than Candida has not been established.

2 DOSAGE AND ADMINISTRATION

2.1 Dosage for Adults

The recommended dosage for adult patients based on indications are shown in Table 1.

Table 1. MYCAMINE Dosage in Adult Patients
Indication | Recommended Reconstituted Dose Once Daily
Treatment of Candidemia, Acute Disseminated Candidiasis, Candida Peritonitis and Abscesses [In patients treated successfully for candidemia and other Candida infections, the mean duration of treatment was 15 days (range 10 to 47 days).] | 100 mg
Treatment of Esophageal Candidiasis [In patients treated successfully for esophageal candidiasis, the mean duration of treatment was 15 days (range 10 to 30 days).] | 150 mg
Prophylaxis of Candida Infections in HSCT Recipients [In hematopoietic stem cell transplant (HSCT) recipients who experienced success of prophylactic therapy, the mean duration of prophylaxis was 19 days (range 6 to 51 days).] | 50 mg

2.2 Dosage for Pediatric Patients 4 Months and Older

The recommended dosage for pediatric patients 4 months of age and older based on indication and weight are shown in Table 2.

Table 2. MYCAMINE Dosage in Pediatric Patients (4 Months of Age and Older)
Indication | Dosage for Pediatric Patients; 4 Months of Age and Older
Indication | 30 kg or less | Greater than 30 kg
Treatment of Candidemia, Acute Disseminated Candidiasis, Candida Peritonitis and Abscesses | 2 mg/kg once daily; (maximum daily dose 100 mg)
Treatment of Esophageal Candidiasis | 3 mg/kg once daily | 2.5 mg/kg once daily (maximum daily dose 150 mg)
Prophylaxis of Candida Infections in HSCT Recipients | 1 mg/kg once daily (maximum daily dose 50 mg)

2.3 Dosage for Pediatric Patients Younger than 4 Months of Age

Treatment of Candidemia, Acute Disseminated Candidiasis, Candida Peritonitis and Abscesses without meningoencephalitis and/or ocular dissemination
The recommended dosage is 4 mg/kg once daily.
The safety and effectiveness of MYCAMINE have not been established for the treatment of candidemia with meningoencephalitis and/or ocular dissemination in pediatric patients younger than 4 months of age as a higher dose may be needed [see Use in Specific Populations (8.4), Clinical Pharmacology (12.3) and Microbiology (12.4)].

2.4 Directions for Reconstitution, Dilution, and Preparation

Do not mix or co-infuse MYCAMINE with other medications. MYCAMINE has been shown to precipitate when mixed directly with a number of other commonly used medications. Please read this entire section carefully before beginning reconstitution.

Reconstitution

Reconstitute MYCAMINE vials by aseptically adding 5 mL of one of the following compatible solutions:

- 0.9% Sodium Chloride Injection, USP (without a bacteriostatic agent)
- 5% Dextrose Injection, USP

To minimize excessive foaming, gently dissolve the MYCAMINE powder by swirling the vial. Do not vigorously shake the vial. Visually inspect the vial for particulate matter.

MYCAMINE 50 mg vial: after reconstitution each mL contains 10 mg of micafungin.
MYCAMINE 100 mg vial: after reconstitution each mL contains 20 mg of micafungin.

Parenteral drug products should be inspected visually for particulate matter and discoloration prior to administration, whenever solution and container permit. Do not use if there is any evidence of precipitation or foreign matter. Aseptic technique must be strictly observed in all handling since no preservative or bacteriostatic agent is present in MYCAMINE or in the materials specified for reconstitution and dilution.

The reconstituted product should be protected from light and may be stored in the original vial for up to 24 hours at room temperature, 25oC (77oF).

Dilution and Preparation

The diluted solution should be protected from light. It is not necessary to cover the infusion drip chamber or the tubing.

Adult Patients:

1. Add the appropriate volume of reconstituted MYCAMINE into 100 mL of 0.9% Sodium Chloride Injection, USP or 100 mL of 5% Dextrose Injection, USP.
2. Appropriately label the bag.

Pediatric Patients

1. Calculate the total MYCAMINE dose in milligrams (mg) by multiplying the recommended pediatric dose (mg/kg) for a given indication [see Table 2] and the weight of the patient in kilograms (kg).
2. To calculate the volume (mL) of drug needed, divide the calculated dose (mg) from step 1 by the final concentration of the selected reconstituted vial(s) (either 10 mg/mL for the 50 mg vial or 20 mg/mL for the
  100 mg vial), see example below:
  Using 50 mg vials:
  Divide the calculated mg dose (from step 1) by 10 mg/mL to determine the volume (mL) needed.
  OR
  Using 100 mg vials:
  Divide the calculated mg dose (from step 1) by 20 mg/mL to determine the volume (mL) needed.
3. Withdraw the calculated volume (mL) of drug needed from the selected concentration and size of reconstituted MYCAMINE vial(s) used in Step 2 (ensure the selected concentration and vial size used to calculate the dose is also used to prepare the infusion).
4. Add the withdrawn volume of drug (step 3) to a 0.9% Sodium Chloride Injection, USP or 5% Dextrose Injection, USP intravenous infusion bag or syringe. Ensure that the final concentration of the solution is between 0.5 mg/mL to 4 mg/mL.
  To decrease the risk of infusion reactions, concentrations above 1.5 mg/mL should be administered via central catheter [see Warnings and Precautions (5.5)].
5. Appropriately label the infusion bag or syringe. For concentrations above 1.5 mg/mL, if required, label to specifically warn to administer the solution via central catheter.

The diluted infusion bag should be protected from light and may be stored for up to 24 hours at room temperature, 25oC (77oF).

MYCAMINE is preservative-free. Discard partially used vials.

2.5 Infusion Volume and Duration

Administer MYCAMINE by intravenous infusion only. Infuse over one hour. More rapid infusions may result in more frequent histamine-mediated reactions [see Warnings and Precautions (5.5)].

Flush an existing intravenous line with 0.9% Sodium Chloride Injection, USP, prior to infusion of MYCAMINE.

Pediatric Patients

MYCAMINE should be infused over one hour. To decrease the risk of infusion reactions, concentrations above
1.5 mg/mL should be administered via central catheter [see Warnings and Precautions (5.5)].

3 DOSAGE FORMS AND STRENGTHS

MYCAMINE is a sterile, white lyophilized powder for reconstitution for intravenous infusion available as:

- 50 mg single-dose vial
- 100 mg single-dose vial

4 CONTRAINDICATIONS

MYCAMINE is contraindicated in persons with known hypersensitivity to micafungin, any component of MYCAMINE, or other echinocandins.

5 WARNINGS AND PRECAUTIONS

5.1 Hypersensitivity Reactions

Isolated cases of serious hypersensitivity (anaphylaxis and anaphylactoid) reactions (including shock) have been reported in patients receiving MYCAMINE. If these reactions occur, MYCAMINE infusion should be discontinued and appropriate treatment administered.

5.2 Hematological Effects

Acute intravascular hemolysis and hemoglobinuria was seen in a healthy volunteer during infusion of MYCAMINE (200 mg) and oral prednisolone (20 mg). Cases of significant hemolysis and hemolytic anemia have also been reported in patients treated with MYCAMINE. Patients who develop clinical or laboratory evidence of hemolysis or hemolytic anemia during MYCAMINE therapy should be monitored closely for evidence of worsening of these conditions and evaluated for the risk/benefit of continuing MYCAMINE therapy.

5.3 Hepatic Effects

Laboratory abnormalities in liver function tests have been seen in healthy volunteers and patients treated with MYCAMINE. In some patients with serious underlying conditions who were receiving MYCAMINE along with multiple concomitant medications, clinical hepatic abnormalities have occurred, and isolated cases of significant hepatic impairment, hepatitis, and hepatic failure have been reported. Patients who develop abnormal liver function tests during MYCAMINE therapy should be monitored for evidence of worsening hepatic function and evaluated for the risk/benefit of continuing MYCAMINE therapy.

5.4 Renal Effects

Elevations in BUN and creatinine, and isolated cases of significant renal impairment or acute renal failure have been reported in patients who received MYCAMINE. In fluconazole-controlled trials, the incidence of drug-related renal adverse reactions was 0.4% for MYCAMINE-treated patients and 0.5% for fluconazole-treated patients. Patients who develop abnormal renal function tests during MYCAMINE therapy should be monitored for evidence of worsening renal function.

5.5 Infusion and Injection Site Reactions

Possible histamine-mediated symptoms have been reported with MYCAMINE, including rash, pruritus, facial swelling, and vasodilatation. Slow the infusion rate if infusion reaction occurs [see Dosage and Administration (2.3)].

Injection site reactions, including phlebitis and thrombophlebitis have been reported, at MYCAMINE doses of 50 to 150 mg/day. These reactions tended to occur more often in patients receiving MYCAMINE via peripheral intravenous administration [see Dosage and Administration (2.3) and Adverse Reactions (6.1)].

6 ADVERSE REACTIONS

The following clinically significant adverse reactions are described elsewhere in the labeling:

- Hypersensitivity Reactions [see Warnings and Precautions (5.1)]
- Hematological Effects [see Warnings and Precautions (5.2)]
- Hepatic Effects [see Warnings and Precautions (5.3)]
- Renal Effects [see Warnings and Precautions (5.4)]
- Infusion and Injection Site Reactions [see Warnings and Precautions (5.5)]

6.1 Clinical Trials Experience

Because clinical trials are conducted under widely varying conditions, adverse reaction rates observed in clinical trials of MYCAMINE cannot be directly compared to rates in clinical trials of another drug and may not reflect the rates observed in practice.

The overall safety of MYCAMINE was assessed in 520 healthy volunteers and 3417 adult and pediatric patients who received single or multiple doses of MYCAMINE across 50 clinical trials, including the invasive candidiasis, esophageal candidiasis and prophylaxis trials. The doses of MYCAMINE administered included doses above and below the recommended doses [see Dosage and Administration (2.1, 2.2)] and ranged from 0.75 mg/kg to 15 mg/kg in pediatric patients and 12.5 mg to 150 mg/day or greater in adults.

Clinical Trials Experience in Adults

In clinical trials with MYCAMINE, 2497/2748 (91%) adult patients experienced at least one adverse reaction.

Candidemia and Other Candida Infections

In a randomized, double-blind trial for the treatment of candidemia and other Candida infections, adverse reactions occurred in 183/200 (92%) and 171/193 (89%) patients in the MYCAMINE 100 mg/day, and caspofungin (70 mg loading dose followed by 50 mg/day dose) treatment groups, respectively. Selected adverse reactions occurring in 5% or more of the patients and more frequently in the MYCAMINE treatment group, are shown in Table 3.

Table 3. Selected [During IV treatment + 3 days.] Adverse Reactions in Adult Patients with Candidemia and Other Candida Infections
Adverse Reactions by System Organ Class [Within a system organ class, patients may experience more than 1 adverse reaction.] | MYCAMINE 100 mg; n (%) | Caspofungin [70 mg loading dose on day 1 followed by 50 mg/day thereafter (caspofungin).]; n (%)
Number of Patients | 200 | 193
Gastrointestinal Disorders | 81 (41) | 76 (39)
Diarrhea | 15 (8) | 14 (7)
Vomiting | 18 (9) | 16 (8)
Metabolism and Nutrition Disorders | 77 (39) | 73 (38)
Hypoglycemia | 12 (6) | 9 (5)
Hyperkalemia | 10 (5) | 5 (3)
General Disorders/Administration Site Conditions | 59 (30) | 51 (26)
Investigations | 36 (18) | 37 (19)
Blood Alkaline Phosphatase Increased | 11 (6) | 8 (4)
Cardiac Disorders | 35 (18) | 36 (19)
Atrial Fibrillation | 5 (3) | 0
Patient base: all randomized patients who received at least 1 dose of trial drug.

In a second, supportive, randomized, double-blind trial for the treatment of candidemia and other Candida infections, adverse reactions occurred in 245/264 (93%) and 250/265 (94%) adult and pediatric patients in the MYCAMINE (100 mg/day) and amphotericin B liposome (3 mg/kg/day) treatment groups, respectively. In this trial, the following adverse reactions were reported in patients at least 16 years of age in the MYCAMINE and amphotericin B liposome treatment groups, respectively: nausea (10% vs. 8%), diarrhea (11% vs. 11%), vomiting (13% vs. 9%), abnormal liver tests (4% vs. 3%), increased aspartate aminotransferase (3% vs. 2%), and increased blood alkaline phosphatase
(3% vs. 2%).

Esophageal Candidiasis

In a randomized, double-blind study for treatment of esophageal candidiasis, a total of 202/260 (78%) patients who received MYCAMINE 150 mg/day and 186/258 (72%) patients who received intravenous fluconazole 200 mg/day experienced an adverse reaction. Adverse reactions resulting in discontinuation were reported in 17 (7%) MYCAMINE-treated patients; and in 12 (5%) fluconazole-treated patients. Selected treatment-emergent adverse reactions occurring in 5% or more of the patients and more frequently in the MYCAMINE group, are shown in Table 4.

Table 4. Selected [During treatment + 3 days.] Adverse Reactions in Adult Patients with Esophageal Candidiasis
Adverse Reactions by System Organ Class [Within a system organ class, patients may experience more than 1 adverse reaction.] | MYCAMINE; 150 mg/day; n (%) | Fluconazole; 200 mg/day; n (%)
Number of Patients | 260 | 258
Gastrointestinal Disorders | 84 (32) | 93 (36)
Diarrhea | 27 (10) | 29 (11)
Nausea | 20 (8) | 23 (9)
Vomiting | 17 (7) | 17 (7)
General Disorders/Administration Site Conditions | 52 (20) | 45 (17)
Pyrexia | 34 (13) | 21 (8)
Nervous System Disorders | 42 (16) | 40 (16)
Headache | 22 (9) | 20 (8)
Vascular Disorders | 54 (21) | 21 (8)
Phlebitis | 49 (19) | 13 (5)
Skin and Subcutaneous Tissue Disorders | 36 (14) | 26 (10)
Rash | 14 (5) | 6 (2)
Patient base: all randomized patients who received at least 1 dose of trial drug.

Prophylaxis of Candida Infections in Hematopoietic Stem Cell Transplant Recipients

A double-blind trial was conducted in a total of 882 patients scheduled to undergo an autologous or allogeneic hematopoietic stem cell transplant. The median duration of treatment was 18 days (range 1 to 51 days) in both treatment arms.

All adult patients who received MYCAMINE (382) or fluconazole (409) experienced at least one adverse reaction during the study. Treatment-emergent adverse reactions resulting in MYCAMINE discontinuation were reported in 15 (4%) adult patients; while those resulting in fluconazole discontinuation were reported in 32 (8%). Selected adverse reactions reported in 15% or more of adult patients and more frequently in the MYCAMINE treatment arm, are shown in Table 5.

Table 5. Selected Adverse Reactions in Adult Patients During Prophylaxis of Candida Infection in Hematopoietic Stem Cell Transplant Recipients
System Organ Class | MYCAMINE; 50 mg/day; n (%) | Fluconazole; 400 mg/day; n (%)
Number of Patients | 382 | 409
Gastrointestinal Disorders | 377 (99) | 404 (99)
Diarrhea | 294 (77) | 327 (80)
Nausea | 270 (71) | 290 (71)
Vomiting | 252 (66) | 274 (67)
Abdominal Pain | 100 (26) | 93 (23)
Blood and Lymphatic System Disorders | 368 (96) | 385 (94)
Neutropenia | 288 (75) | 297 (73)
Thrombocytopenia | 286 (75) | 280 (69)
Skin and Subcutaneous Tissue Disorders | 257 (67) | 275 (67)
Rash | 95 (25) | 91 (22)
Nervous System Disorders | 250 (65) | 254 (62)
Headache | 169 (44) | 154 (38)
Psychiatric Disorders | 233 (61) | 235 (58)
Insomnia | 142 (37) | 140 (34)
Anxiety | 84 (22) | 87 (21)
Cardiac Disorders | 133 (35) | 138 (34)
Tachycardia | 99 (26) | 91 (22)
Patient base: all randomized adult patients who received at least 1 dose of trial drug.

Other selected adverse reactions reported at less than 5% in adult clinical trials are listed below:

- Blood and lymphatic system disorders: coagulopathy, pancytopenia, thrombotic thrombocytopenic purpura
- Cardiac disorders: cardiac arrest, myocardial infarction, pericardial effusion
- General disorders and administration site conditions: infusion reaction, injection site thrombosis
- Hepatobiliary disorders: hepatocellular damage, hepatomegaly, jaundice, hepatic failure
- Immune disorders: hypersensitivity, anaphylactic reaction
- Metabolism and nutrition disorders: hypernatremia, hypokalemia
- Nervous system disorders: convulsions, encephalopathy, intracranial hemorrhage
- Psychiatric disorders: delirium
- Skin and subcutaneous tissue disorders: urticaria

Clinical Trials Experience in Pediatric Patients

The safety of MYCAMINE was assessed in 593 pediatric patients, 425 of whom were 4 months through 16 years of age and 168 of whom were 3 days to less than 4 months of age who received at least one dose of MYCAMINE across 15 clinical trials.

Of the 425 pediatric patients, 4 months through 16 years of age enrolled in 11 clinical trials, 235 (55%) were male, 290 (68%) were white, with the following age distribution: 62 (15%) 4 months to <2 years, 108 (25%) 2 to 5 years, 140 (33%) 6 to 11 years, and 115 (27%) 12 to 16 years of age. The mean treatment duration was 26.1 days. A total of 246 patients received at least one dose of MYCAMINE ranging from 2 to 10 mg/kg. Overall, 388/425 (91%) patients experienced at least one adverse reaction. Adverse reactions occurring in ≥15% or more of micafungin-treated pediatric patients 4 months of age and older are: vomiting (32%), diarrhea (24%), pyrexia (24%), hypokalemia (22%), nausea (21%), mucosal inflammation (19%), thrombocytopenia (19%), abdominal pain (18%), headache (15%), and hypertension (15%).

Two randomized, double-blind active-controlled trials included pediatric patients. In the invasive candidiasis/candidemia trial, the efficacy and safety of MYCAMINE (2 mg/kg/day for patients weighing 40 kg or less and 100 mg/day for patients weighing greater than 40 kg) was compared to amphotericin B liposome (3 mg/kg/day) in 112 pediatric patients. Treatment-emergent adverse reactions occurred in 51/56 (91%) of patients in the MYCAMINE group and 52/56 (93%) of patients in the amphotericin B liposome group. Treatment-emergent adverse reactions resulting in drug discontinuation were reported in 2 (4%) MYCAMINE-treated pediatric patients and in 9 (16%) amphotericin B liposome-treated pediatric patients.

The prophylaxis study in patients undergoing HSCT investigated the efficacy of MYCAMINE (1 mg/kg/day for patients weighing 50 kg or less and 50 mg/day for patients weighing greater than 50 kg) as compared to fluconazole (8 mg/kg/day for patients weighing 50 kg or less and 400 mg/day for patients weighing greater than 50 kg). All 91 pediatric patients experienced at least one treatment-emergent adverse reaction. Three (7%) pediatric patients discontinued MYCAMINE due to adverse reaction, while one (2%) patient discontinued fluconazole.

Selected adverse reactions, occurring in 15% or more of the patients and more frequently in a MYCAMINE group, for the two comparative trials are shown in Table 6.

Table 6. Selected Adverse Reactions in Pediatric Patients with Candidemia and Other Candida Infections (C/IC), and in Hematopoietic Stem-Cell Recipients During Prophylaxis of Candida Infections
Adverse Reactions [Within a system organ class, patients may experience more than 1 adverse reaction.] | C/IC [Study population included 20 pediatric patients younger than 4 months of age (10 in each arm)] |  | Prophylaxis
Adverse Reactions [Within a system organ class, patients may experience more than 1 adverse reaction.] | MYCAMINE n = 56 n (%) | Amphotericin B liposome n = 56 n (%) | MYCAMINE n = 43 n (%) | Fluconazole n = 48 n (%)
Gastrointestinal disorders | 22 (40) | 18 (32) | 43 (100) | 45 (94)
Vomiting | 10 (18) | 8 (14) | 28 (65) | 32 (67)
Diarrhea | 4 (7) | 5 (9) | 22 (51) | 31 (65)
Nausea | 4 (7) | 4 (7) | 30 (70) | 25 (52)
Abdominal pain | 2 (4) | 2 (4) | 15 (35) | 12 (25)
Abdominal distension | 1 (2) | 1 (2) | 8 (19) | 6 (13)
General disorders and administration site conditions | 14 (25) | 14 (25) | 41 (95) | 46 (96)
Pyrexia | 5 (9) | 9 (16) | 26 (61) | 31 (65)
Infusion-related reaction | 0 | 3 (5) | 7 (16) | 4 (8)
Skin and subcutaneous tissue disorders | 11 (20) | 8 (14) | 33 (77) | 38 (79)
Pruritus | 0 | 1 (2) | 14 (33) | 15 (31)
Rash | 1 (2) | 1 (2) | 13 (30) | 13 (27)
Urticaria | 0 | 1 (2) | 8 (19) | 4 (8)
Respiratory, thoracic and mediastinal disorders | 9 (16) | 13 (23) | 30 (70) | 33 (69)
Epistaxis | 0 | 0 | 4 (9) | 8 (17)
Blood and lymphatic system disorders | 17 (30) | 13 (23) | 40 (93) | 44 (92)
Thrombocytopenia | 5 (9) | 3 (5) | 31 (72) | 37 (77)
Neutropenia | 3 (5) | 4 (7) | 33 (77) | 34 (71)
Anemia | 10 (18) | 6 (11) | 22 (51) | 24 (50)
Febrile neutropenia | 0 | 0 | 7 (16) | 7 (15)
Investigations | 12 (21) | 8 (14) | 24 (56) | 25 (52)
Alanine aminotransferase increased | 0 | 0 | 7 (16) | 1 (2)
Urine output decreased | 0 | 0 | 10 (23) | 8 (17)
Cardiac disorders | 7 (13) | 3 (5) | 10 (23) | 17 (35)
Tachycardia | 2 (4) | 1 (2) | 7 (16) | 12 (25)
Renal and urinary disorders | 4 (7) | 4 (7) | 16 (37) | 15 (31)
Hematuria | 0 | 0 | 10 (23) | 7 (15)
Psychiatric disorders | 3 (5) | 1 (2) | 20 (47) | 9 (19)
Anxiety | 0 | 0 | 10 (23) | 3 (6)

Other clinically significant adverse reactions reported at less than 15% in pediatric clinical trials are listed below:

- Hepatobiliary disorders: hyperbilirubinemia
- Investigations: liver tests abnormal
- Renal Disorders: renal failure

Clinical Trials Experience in Pediatric Patients Younger than 4 Months of Age

The safety of MYCAMINE was assessed in 168 pediatric patients younger than 4 months of age who received varying doses of MYCAMINE in 9 clinical trials. The mean treatment duration was 16.6 days. A total of 59 patients received MYCAMINE at doses ≤4 mg/kg/day and 109 patients received MYCAMINE doses >4 mg/kg/day [5 to 15 mg/kg/day (approximately 1.3 to 3.8 times the recommended dosage in pediatric patients less than 4 months old)].

The adverse reaction profile of MYCAMINE in pediatric patients younger than 4 months of age was generally comparable to that of pediatric patients 4 months of age and older and adults. The most frequent adverse reactions (≥15%) in pediatric patients younger than 4 months old receiving a MYCAMINE dose of approximately 4 mg/kg/day included hypokalemia (25%), thrombocytopenia (25%), acidosis (20%), sepsis (20%), anemia (15%), oxygen saturation decreased (15%), and vomiting (15%). No new safety signals were seen in patients who received 5 to 15 mg/kg/day [see Use in Specific Populations (8.4)].

Additional clinically significant adverse reactions reported in less than 15% of pediatric patients younger than 4 months of age who received approximately 4 mg/kg/day are listed below:

- Blood and Lymphatic System Disorders: leukocytosis, thrombocytosis, coagulation disorder neonatal
- Gastrointestinal Disorders: hematochezia, intestinal perforation, ascites, ileus, intestinal infarction, diarrhea, abdominal distension
- General Disorders and Administration Site Conditions: peripheral swelling, generalized edema, pyrexia, infusion site extravasation, edema neonatal
- Hepatobiliary Disorders: hyperbilirubinemia
- Investigations: blood lactate dehydrogenase increased, blood urea increased, ECG QRS complex prolonged
- Vascular Disorders: neonatal hypotension, thrombophlebitis
- Musculoskeletal and connective tissue disorders: hypertonia neonatal
- Respiratory, thoracic and mediastinal disorders: pleural effusion, respiratory failure, neonatal aspiration, respiratory distress
- Metabolism and nutrition disorders: hyperglycemia, dehydration, hypocalcemia, hypermagnesemia

6.2 Postmarketing Experience

The following adverse reactions have been identified during post-approval use of micafungin for injection. Because these reactions are reported voluntarily from a population of uncertain size, it is not always possible to reliably estimate their frequency or establish a causal relationship to drug exposure.

- Blood and lymphatic system disorders: disseminated intravascular coagulation
- Hepatobiliary disorders: hepatic disorder
- Renal and urinary disorders: renal impairment
- Skin and subcutaneous tissue disorders: Stevens-Johnson syndrome, toxic epidermal necrolysis
- Vascular disorders: shock

7 DRUG INTERACTIONS

7.1 Effect of Other Drugs on MYCAMINE

CYP3A4, CYP2C9 and CYP2C19 Inhibitors

Co-administration of MYCAMINE with cyclosporine, itraconazole, voriconazole and fluconazole did not alter the pharmacokinetics of MYCAMINE.

CYP2C19 and CYP3A4 Inducer

Co-administration of MYCAMINE with rifampin and ritonavir did not alter the pharmacokinetics of MYCAMINE.

Co-administration of MYCAMINE with Other Drugs

Co-administration of MYCAMINE with mycophenolate mofetil (MMF), amphotericin B, tacrolimus, prednisolone, sirolimus and nifedipine did not alter the pharmacokinetics of MYCAMINE.

7.2 Effect of MYCAMINE on Other Drugs

CYP3A4 Substrates

There was no effect of single or multiple doses of MYCAMINE on cyclosporine, tacrolimus, prednisolone, voriconazole and fluconazole pharmacokinetics.

Sirolimus AUC was increased by 21% with no effect on Cmax in the presence of steady-state MYCAMINE compared with sirolimus alone. Nifedipine AUC and Cmax were increased by 18% and 42%, respectively, in the presence of steady-state MYCAMINE compared with nifedipine alone. Itraconazole AUC and Cmax were increased by 22% and 11%, respectively. Patients receiving sirolimus, nifedipine, and itraconazole in combination with MYCAMINE should be monitored for sirolimus, nifedipine, and itraconazole toxicity and the sirolimus, nifedipine, and itraconazole dosage should be reduced if necessary.

UDP-Glycosyltransferase Substrate

Co-administration of mycophenolate mofetil (MMF) with MYCAMINE did not alter the pharmacokinetics of MMF.

8 USE IN SPECIFIC POPULATIONS

8.1 Pregnancy

Risk Summary

Based on findings from animal studies, MYCAMINE may cause fetal harm when administered to a pregnant woman (see Data). There is insufficient human data on the use of MYCAMINE in pregnant women to inform a drug-associated risk of adverse developmental outcomes. In animal reproduction studies, intravenous administration of micafungin sodium to pregnant rabbits during organogenesis at doses four times the maximum recommended human dose resulted in visceral abnormalities and increased abortion (see Data). Advise pregnant women of the risk to the fetus.

The estimated background risk of major birth defects and miscarriage for the indicated populations is unknown. All pregnancies have a background risk of birth defect, loss, or other adverse outcomes. In the U.S. general population, the estimated background risk of major birth defects and miscarriage in clinically recognized pregnancies is 2 to 4% and 15 to 20%, respectively.

Data

Animal Data

In an embryo-fetal toxicity study in pregnant rabbits, intravenous administration of micafungin sodium during organogenesis (days 6 to 18 of gestation) resulted in fetal visceral abnormalities and abortion at 32 mg/kg, a dose equivalent to four times the recommended human dose based on body surface area comparisons. Visceral abnormalities included abnormal lobation of the lung, levocardia, retrocaval ureter, anomalous right subclavian artery, and dilatation of the ureter.

8.2 Lactation

Risk Summary

There are no data on the presence of micafungin in human milk, the effects on the breast-fed infant or the effects on milk production. Micafungin was present in the milk of lactating rats following intravenous administration. When a drug is present in animal milk, it is likely that the drug will be present in human milk. The developmental and health benefits of breastfeeding should be considered along with the mother’s clinical need for MYCAMINE, and any potential adverse effects on the breast-fed child from MYCAMINE, or from the underlying maternal condition.

8.4 Pediatric Use

Pediatric Patients 4 Months of Age and Older

The safety and effectiveness of MYCAMINE for the treatment of esophageal candidiasis, candidemia, acute disseminated candidiasis, Candida peritonitis and abscesses, esophageal candidiasis, and for prophylaxis of Candida infections in patients undergoing HSCT have been established in pediatric patients 4 months of age and older. Use of MYCAMINE for these indications and in this age group is supported by evidence from adequate and well-controlled studies in adult and pediatric patients with additional pharmacokinetic and safety data in pediatric patients 4 months of age and older [see Indications and Usage (1), Adverse Reactions (6.1), Clinical Pharmacology (12.3), and Clinical Studies (14)].

Pediatric Patients Younger than 4 Months of Age

Treatment of Candidemia, Acute Disseminated Candidiasis, Candida Peritonitis and Abscesses Without Meningoencephalitis and/or Ocular Dissemination in Pediatric Patients Younger Than 4 Months of Age

The safety and effectiveness of MYCAMINE for the treatment of candidemia, acute disseminated candidiasis, Candida peritonitis and abscesses without meningoencephalitis and/or ocular dissemination at a dosage of 4 mg/kg once daily have been established in pediatric patients younger than 4 months of age. This use and dosage of MYCAMINE are supported by evidence from adequate and well-controlled studies in adult and pediatric patients 4 months of age and older with additional pharmacokinetic and safety data in pediatric patients younger than 4 months of age [see Adverse Reactions (6.1) and Clinical Pharmacology (12.3)].

Treatment of Candidemia, Acute Disseminated Candidiasis, Candida Peritonitis and Abscesses With Meningoencephalitis and/or Ocular Dissemination in Pediatric Patients Younger Than 4 Months of Age

The safety and effectiveness of MYCAMINE have not been established for the treatment of candidemia with meningoencephalitis and/or ocular dissemination in pediatric patients younger than 4 months of age.

In a rabbit model of hematogenous Candida meningoencephalitis (HCME) with Candida albicans (minimum inhibitory concentration of 0.125 mcg/mL), a decrease in mean fungal burden in central nervous system (CNS) compartments assessed as the average of combined fungal burden in the cerebrum, cerebellum, and spinal cord relative to untreated controls, was observed with increasing micafungin dosages administered once daily for 7 days. Data from the rabbit model suggest that a micafungin dose regimen of 4 mg/kg once daily is inadequate to treat meningoencephalitis and that a dose regimen of approximately 10 to 25 mg/kg once daily may be necessary to lower fungal burden in the CNS in pediatric patients younger than 4 months of age [see Microbiology (12.4)]. In this rabbit model, micafungin concentrations could not be reliably detected in cerebrospinal fluid (CSF). Due to limitations of the study design, the clinical significance of a decreased CNS fungal burden in the rabbit HCME model is uncertain.

A randomized controlled trial evaluated a MYCAMINE dose regimen of 10 mg/kg once daily in pediatric patients younger than 4 months of age with suspected or proven Candida meningoencephalitis. Fungal-free survival at 1 week after end of therapy was observed in 60% of MYCAMINE-treated vs. 70% of amphotericin B-treated patients, and all-cause mortality was 15% vs. 10%, respectively. However, because this study was terminated early and enrolled only 30 pediatric patients younger than 4 months of age (20 treated with MYCAMINE and 10 treated with amphotericin B) which was 13% of the planned enrollment for the study, no conclusions can be drawn regarding efficacy of MYCAMINE at this dose regimen.

In six uncontrolled, open-label studies, and a neonatal intensive care unit (ICU) medical records database, pediatric patients younger than 4 months of age with suspected Candida meningoencephalitis or disseminated candidemia received MYCAMINE at dose regimens ranging from 5 to 15 mg/kg once daily. Across the entire MYCAMINE development program, only 6 pediatric patients with proven Candida meningoencephalitis were treated with dosages of 2 mg/kg, 8 mg/kg and 10 mg/kg once daily. Micafungin was detected in the CSF of pediatric patients with suspected Candida meningoencephalitis. No conclusions regarding the efficacy of a particular dosage of MYCAMINE or the penetration of micafungin into the CSF can be drawn due to limitations of the data, including but not limited to, multiple confounding factors, variable study designs, and limited numbers of patients. No new safety signals were observed with the use of MYCAMINE at dosages of 5 to 15 mg/kg once daily in pediatric patients younger than 4 months of age, and there was no discernible dose-response for adverse events.

Although the dosage for the treatment of candidemia with meningoencephalitis has not been established, antifungal activity in various CNS compartments in the rabbit HCME model and limited clinical trial data suggest that in patients younger than 4 months of age, dose regimens 10 mg/kg once daily or higher may be necessary for the treatment of candidemia with meningoencephalitis. Safety data from clinical studies for MYCAMINE at dose regimens of 10 to 15 mg/kg once daily in pediatric patients younger than 4 months of age did not reveal new safety signals.

Treatment of Esophageal Candidiasis and Prophylaxis of Candida Infections in Patients Undergoing Hematopoietic Stem Cell Transplantation in Pediatric Patients Younger Than 4 Months of Age

The safety and effectiveness of MYCAMINE in pediatric patients younger than 4 months of age have not been established for the:

- Treatment of esophageal candidiasis
- Prophylaxis of Candida infections in patients undergoing hematopoietic stem cell transplantation

8.5 Geriatric Use

A total of 418 subjects in clinical studies of MYCAMINE were 65 years of age and older, and 124 subjects were 75 years of age and older. No overall differences in safety and effectiveness were observed between these subjects and younger subjects. Other reported clinical experience has not identified differences in responses between the elderly and younger patients, but greater sensitivity of some older individuals cannot be ruled out.

The exposure and disposition of a 50 mg MYCAMINE dose administered as a single 1-hour infusion to 10 healthy subjects aged 66 to 78 years were not significantly different from those in 10 healthy subjects aged 20 to 24 years. No dose adjustment is necessary for the elderly.

8.6 Use in Patients with Renal Impairment

MYCAMINE does not require dose adjustment in patients with renal impairment. Supplementary dosing should not be required following hemodialysis [see Clinical Pharmacology (12.3)].

8.7 Use in Patients with Hepatic Impairment

Dose adjustment of MYCAMINE is not required in patients with mild, moderate, or severe hepatic impairment [see Clinical Pharmacology (12.3)].

8.8 Race and Gender

No dose adjustment of MYCAMINE is required based on gender or race. After 14 daily doses of 150 mg to healthy subjects, micafungin AUC in women was greater by approximately 23% compared with men, due to smaller body weight. No notable differences among white, black, and Hispanic subjects were seen. The micafungin AUC was greater by 19% in Japanese subjects compared to blacks, due to smaller body weight.

9 DRUG ABUSE AND DEPENDENCE

There has been no evidence of either psychological or physical dependence or withdrawal or rebound effects with MYCAMINE.

10 OVERDOSAGE

MYCAMINE is highly protein bound and, therefore, is not dialyzable. No cases of MYCAMINE overdosage have been reported. Repeated daily doses up to 8 mg/kg (maximum total dose of 896 mg) in adult patients, up to 6 mg/kg in pediatric patients 4 months of age and older, and up to 15 mg/kg in pediatric patients younger than 4 months of age have been administered in clinical trials with no reported dose-limiting toxicity [see Adverse Reactions (6.1) and Use in Specific Populations (8.4)].

11 DESCRIPTION

MYCAMINE is a sterile, lyophilized product for intravenous (IV) infusion that contains micafungin sodium. Micafungin sodium is a semisynthetic lipopeptide (echinocandin) synthesized by a chemical modification of a fermentation product of Coleophoma empetri F-11899. Micafungin inhibits the synthesis of 1,3-beta-D-glucan, an integral component of the fungal cell wall.

Each single-dose vial contains 50 mg micafungin (equivalent to 50.86 mg micafungin sodium) or 100 mg micafungin (equivalent to 101.73 mg micafungin sodium), 200 mg lactose monohydrate, with citric acid and/or sodium hydroxide (used for pH adjustment). MYCAMINE must be diluted with 0.9% Sodium Chloride Injection, USP, or 5% Dextrose Injection, USP [see Dosage and Administration (2)]. Following reconstitution with 0.9% Sodium Chloride Injection, USP, the resulting pH of the solution is between 5-7.

Micafungin sodium is chemically designated as:

Pneumocandin A0,1-[(4R,5R)-4,5-dihydroxy-N^2-[4-[5-[4-(pentyloxy) phenyl]-3-isoxazolyl]benzoyl]-L-ornithine]-4-[(4S)-4-hydroxy-4-[4-hydroxy-3-(sulfooxy)phenyl]-L-threonine]-, monosodium salt.

The chemical structure of micafungin sodium is:

The empirical/molecular formula is C56H70N9NaO23S and the formula weight is 1292.26.

Micafungin sodium is a light-sensitive, hygroscopic white powder that is freely soluble in water, isotonic sodium chloride solution, N,N-dimethylformamide and dimethylsulfoxide, slightly soluble in methyl alcohol, and practically insoluble in acetonitrile, ethyl alcohol (95%), acetone, diethyl ether and n-hexane.

12 CLINICAL PHARMACOLOGY

12.1 Mechanism of Action

Micafungin is a member of the echinocandin class of antifungal agents [see Microbiology (12.4)].

12.2 Pharmacodynamics

The pharmacodynamics of micafungin related to hematogenous Candida meningoencephalitis are described in other sections of the prescribing information [see Use in Specific Populations (8.4) and Microbiology (12.4)].

12.3 Pharmacokinetics

Adults

The pharmacokinetics of micafungin were determined in healthy subjects, hematopoietic stem cell transplant recipients, and patients with esophageal candidiasis up to a maximum daily dose of 8 mg/kg body weight.

The relationship of area under the concentration-time curve (AUC) to micafungin dose was linear over the daily dose range of 50 mg to 150 mg and 3 mg/kg to 8 mg/kg body weight. Typically, 85% of the steady-state concentration is achieved after three daily MYCAMINE doses.

Steady-state pharmacokinetic parameters in relevant patient populations after repeated daily administration are presented in Table 7.

Table 7. Pharmacokinetic Parameters of Micafungin in Adult Patients
Population | n | Dose (mg) | Pharmacokinetic Parameters; (Mean ± Standard Deviation)
Population | n | Dose (mg) | Cmax; (mcg/mL) | AUC0-24 [AUC0-infinity is presented for Day 1; AUC0-24 is presented for steady-state.]; (mcg·h/mL) | t½; (h) | Cl; (mL/min/kg)
Patients with IC [candidemia or other Candida infections.]; [Day 1] | 20 | 100 | 5.7 ± 2.2 | 83 ± 51 | 14.5 ± 7.0 | 0.359 ± 0.179
[Steady-State] | 20 | 100 | 10.1 ± 4.4 | 97 ± 29 | 13.4 ± 2.0 | 0.298 ± 0.115
HIV [human immunodeficiency virus.] - Positive; Patients with EC [esophageal candidiasis.]; [Day 1] | 20; 20; 14 | 50; 100; 150 | 4.1 ± 1.4; 8.0 ± 2.4; 11.6 ± 3.1 | 36 ± 9; 108 ± 31; 151 ± 45 | 14.9 ± 4.3; 13.8 ± 3.0; 14.1 ± 2.6 | 0.321 ± 0.098; 0.327 ± 0.093; 0.340 ± 0.092
[Day 14 or 21] | 20; 20; 14 | 50; 100; 150 | 5.1 ± 1.0; 10.1 ± 2.6; 16.4 ± 6.5 | 54 ± 13; 115 ± 25; 167 ± 40 | 15.6 ± 2.8; 16.9 ± 4.4; 15.2 ± 2.2 | 0.300 ± 0.063; 0.301 ± 0.086; 0.297 ± 0.081
HSCT [hematopoietic stem cell transplant.] Recipients; [Day 7] | 8; 10; 8; 8 | per kg; 3; 4; 6; 8 | 21.1 ± 2.84; 29.2 ± 6.2; 38.4 ± 6.9; 60.8 ± 26.9 | 234 ± 34; 339 ± 72; 479 ± 157; 663 ± 212 | 14.0 ± 1.4; 14.2 ± 3.2; 14.9 ± 2.6; 17.2 ± 2.3 | 0.214 ± 0.031; 0.204 ± 0.036; 0.224 ± 0.064; 0.223 ± 0.081

Pediatric Patients 4 Months of Age and Older

Micafungin pharmacokinetics in 229 pediatric patients 4 months through 16 years of age were characterized using population pharmacokinetics. Micafungin exposure was dose proportional across the dose and age range studied.

Table 8. Summary (Mean +/- Standard Deviation) of Micafungin Pharmacokinetics in Pediatric Patients 4 Months of Age and Older (Steady-State)
Body weight group | N | Dose [Or the equivalent if receiving the adult dose (50, 100, or 150 mg).] mg/kg | Cmax.ss [Derived from simulations from the population PK model.] (mcg/mL) | AUC.ss (mcg·h/mL) | t½ [Derived from the population PK model.] (h) | CL (mL/min/kg)
30 kg or less | 149 | 1.0 | 7.1 +/- 4.7 | 55 +/- 16 | 12.5 +/- 4.6 | 0.328 +/- 0.091
30 kg or less | 149 | 2.0 | 14.2 +/- 9.3 | 109 +/- 31 | 12.5 +/- 4.6 | 0.328 +/- 0.091
30 kg or less | 149 | 3.0 | 21.3 +/- 14.0 | 164 +/- 47 | 12.5 +/- 4.6 | 0.328 +/- 0.091
Greater than 30 kg | 80 | 1.0 | 8.7 +/- 5.6 | 67 +/- 17 | 13.6 +/- 8.8 | 0.241 +/- 0.061
Greater than 30 kg | 80 | 2.0 | 17.5 +/- 11.2 | 134 +/- 33 | 13.6 +/- 8.8 | 0.241 +/- 0.061
Greater than 30 kg | 80 | 2.5 | 23.0 +/- 14.5 | 176 +/- 42 | 13.6 +/- 8.8 | 0.241 +/- 0.061

Pediatric Patients Younger than 4 Months of Age

Micafungin pharmacokinetic data in 103 pediatric patients less than 4 months of age were assessed using population pharmacokinetics. Predicted micafungin AUC estimates were dose proportional across the dose regimens and age ranges studied. The body weight-normalized micafungin clearance in pediatric patients less than 4 months of age is higher than the body weight-normalized micafungin clearance in older pediatric patients greater than 4 months of age and adults. Administration of 4 mg/kg once daily micafungin to pediatric patients less than 4 months of age produces a mean (SD) steady-state AUC of 131 (50) mcg·h/mL, which is comparable to the steady-state AUC in pediatric patients 4 months of age and older administered micafungin 2 mg/kg/day and adults administered 100 mg once daily.

Specific Populations

Adult Patients with Renal Impairment

MYCAMINE does not require dose adjustment in patients with renal impairment. A single 1-hour infusion of 100 mg MYCAMINE was administered to 9 adult subjects with severe renal impairment (creatinine clearance less than 30 mL/min) and to 9 age-, gender-, and weight-matched subjects with normal renal function (creatinine clearance greater than 80 mL/min). The maximum concentration (Cmax) and AUC were not significantly altered by severe renal impairment.

Since micafungin is highly protein bound, it is not dialyzable. Supplementary dosing should not be required following hemodialysis.

Adult Patients with Hepatic Impairment

- A single 1-hour infusion of 100 mg MYCAMINE was administered to 8 adult subjects with moderate hepatic impairment (Child-Pugh score 7 to 9) and 8 age-, gender-, and weight-matched subjects with normal hepatic function. The Cmax and AUC values of micafungin were lower by approximately 22% in subjects with moderate hepatic impairment compared to normal subjects. This difference in micafungin exposure does not require dose adjustment of MYCAMINE in patients with moderate hepatic impairment.
- A single 1-hour infusion of 100 mg MYCAMINE was administered to 8 adult subjects with severe hepatic impairment (Child-Pugh score 10 to 12) and 8 age-, gender-, ethnic- and weight-matched subjects with normal hepatic function. The mean Cmax and AUC values of micafungin were lower by approximately 30% in subjects with severe hepatic impairment compared to normal subjects. The mean Cmax and AUC values of M-5 metabolite were approximately 2.3-fold higher in subjects with severe hepatic impairment compared to normal subjects; however, this exposure (parent and metabolite) was comparable to that in patients with systemic Candida infection. Therefore, no MYCAMINE dose adjustment is necessary in patients with severe hepatic impairment.

Distribution

The mean ± standard deviation volume of distribution of micafungin at terminal phase was 0.39 ± 0.11 L/kg body weight when determined in adult patients with esophageal candidiasis at the dose range of 50 mg to 150 mg.

Micafungin is highly (greater than 99%) protein bound in vitro, independent of plasma concentrations over the range of 10 to 100 mcg/mL. The primary binding protein is albumin; however, micafungin, at therapeutically relevant concentrations, does not competitively displace bilirubin binding to albumin. Micafungin also binds to a lesser extent to α1-acid-glycoprotein.

Micafungin is neither a substrate nor an inhibitor of P-glycoprotein.

Metabolism

Micafungin is metabolized to M-1 (catechol form) by arylsulfatase, with further metabolism to M-2 (methoxy form) by catechol-O-methyltransferase. M-5 is formed by hydroxylation at the side chain (ω-1 position) of micafungin catalyzed by cytochrome P450 (CYP) isozymes. Even though micafungin is a substrate for and a weak inhibitor of CYP3A in vitro, hydroxylation by CYP3A is not a major pathway for micafungin metabolism in vivo. Micafungin is neither a P-glycoprotein substrate nor inhibitor in vitro.

In four healthy volunteer studies, the ratio of metabolite to parent exposure (AUC) at a dose of 150 mg/day was 6% for M-1, 1% for M-2, and 6% for M-5. In patients with esophageal candidiasis, the ratio of metabolite to parent exposure (AUC) at a dose of 150 mg/day was 11% for M-1, 2% for M-2, and 12% for M-5.

Excretion

The excretion of radioactivity following a single intravenous dose of ^14C-micafungin sodium for injection (25 mg) was evaluated in healthy volunteers. At 28 days after administration, mean urinary and fecal recovery of total radioactivity accounted for 82.5% (76.4% to 87.9%) of the administered dose. Fecal excretion is the major route of elimination (total radioactivity at 28 days was 71% of the administered dose).

12.4 Microbiology

Mechanism of Action

Micafungin inhibits the synthesis of 1,3-beta-D-glucan, an essential component of fungal cell walls, which is not present in mammalian cells.

Activity in Animal Models of Candidiasis

Activity of micafungin has been demonstrated in both mucosal and disseminated murine and rabbit models of candidiasis. Micafungin administered to immunocompetent or immunosuppressed mice or rabbits with disseminated candidiasis prolonged survival (mice) and/or decreased the fungal burden in different organs including brain in a dose-dependent manner (mice and rabbits). Overall, antifungal activity of micafungin was demonstrated in the brain and eye tissues of nonneutropenic rabbits with HCME infected with a micafungin-sensitive strain of C. albicans; however, the activity varied in different central nervous system and ocular compartments. In the cerebrum, culture negativity was achieved at a micafungin dose regimen of 32 mg/kg once daily for 7 days; whereas, in spinal cord, vitreous humor, and choroid, culture negativity was achieved at micafungin dose regimens of 24 to 32 mg/kg once daily. Compared to untreated animals, micafungin dose regimens between 8 and 24 mg/kg once daily reduced fungal burden in the cerebrum and cerebellum. When cerebrum, cerebellum and spinal cord data were combined, a decrease in fungal burden relative to untreated controls was evident at micafungin dose regimens between 16 and 32 mg/kg once daily [see Use in Specific Populations (8.4)].

Resistance

There have been reports of clinical failures in patients receiving MYCAMINE therapy due to the development of drug resistance. Some of these reports have identified specific mutations in the FKS protein component of the glucan synthase enzyme that are associated with higher MICs and breakthrough infection.

Antimicrobial Activity

Micafungin has been shown to be active against most isolates of the following Candida species, both in vitro and in clinical infections [see Indications and Usage (1)]:

Candida albicans
Candida glabrata
Candida guilliermondii
Candida krusei
Candida parapsilosis
Candida tropicalis

Susceptibility Testing

For specific information regarding susceptibility test interpretive criteria and associated test methods and quality control standards recognized by FDA for this drug, please see: https://www.fda.gov/STIC.

13 NONCLINICAL TOXICOLOGY

13.1 Carcinogenesis, Mutagenesis, Impairment of Fertility

Hepatic carcinomas and adenomas were observed in a 6-month intravenous toxicology study with an 18-month recovery period of micafungin sodium in rats designed to assess the reversibility of hepatocellular lesions.

Rats administered micafungin sodium for 3 months at 32 mg/kg/day (corresponding to 8 times the highest recommended human dose [150 mg/day], based on AUC comparisons), exhibited colored patches/zones, multinucleated hepatocytes and altered hepatocellular foci after 1 or 3-month recovery periods, and adenomas were observed after a 21-month recovery period. Rats administered micafungin sodium at the same dose for 6 months exhibited adenomas after a 12-month recovery period; after an 18-month recovery period, an increased incidence of adenomas was observed and, additionally, carcinomas were detected. A lower dose of micafungin sodium (equivalent to 5 times the human AUC) in the 6-month rat study resulted in a lower incidence of adenomas and carcinomas following 18 months recovery. The duration of micafungin dosing in these rat studies (3 or 6 months) exceeds the usual duration of MYCAMINE dosing in patients, which is typically less than 1 month for treatment of esophageal candidiasis, but dosing may exceed 1 month for Candida prophylaxis.

Although the increase in carcinomas in the 6-month rat study did not reach statistical significance, the persistence of altered hepatocellular foci subsequent to MYCAMINE dosing, and the presence of adenomas and carcinomas in the recovery periods suggest a causal relationship between micafungin sodium, altered hepatocellular foci, and hepatic neoplasms. Whole-life carcinogenicity studies of MYCAMINE in animals have not been conducted, and it is not known whether the hepatic neoplasms observed in treated rats also occur in other species, or if there is a dose threshold for this effect.

Micafungin sodium was not mutagenic or clastogenic when evaluated in a standard battery of in vitro and in vivo tests (i.e., bacterial reversion - S. typhimurium, E. coli; chromosomal aberration; intravenous mouse micronucleus).

Male rats treated intravenously with micafungin sodium for 9 weeks showed vacuolation of the epididymal ductal epithelial cells at or above 10 mg/kg (about 0.6 times the recommended clinical dose for esophageal candidiasis, based on body surface area comparisons). Higher doses (about twice the recommended clinical dose, based on body surface area comparisons) resulted in higher epididymis weights and reduced numbers of sperm cells. In a 39-week intravenous study in dogs, seminiferous tubular atrophy and decreased sperm in the epididymis were observed at 10 and 32 mg/kg, doses equal to about 2 and 7 times the recommended clinical dose, based on body surface area comparisons. There was no impairment of fertility in animal studies with micafungin sodium.

13.2 Animal Toxicology and/or Pharmacology

High doses of micafungin sodium (5 to 8 times the highest recommended human dose, based on AUC comparisons) have been associated with irreversible changes to the liver when administered for 3 or 6 months, and these changes may be indicative of pre-malignant processes [see Nonclinical Toxicology (13.1)].

14 CLINICAL STUDIES

14.1 Treatment of Candidemia and Other Candida Infections in Adult and Pediatric Patients 4 Months of Age and Older

Two dose levels of MYCAMINE were evaluated in a randomized, double-blind study to determine the efficacy and safety versus caspofungin in patients with invasive candidiasis and candidemia. Patients were randomized to receive once daily intravenous infusions (IV) of MYCAMINE, either 100 mg/day or 150 mg/day or caspofungin (70 mg loading dose followed by 50 mg maintenance dose). Patients in both study arms were permitted to switch to oral fluconazole after at least 10 days of intravenous therapy, provided they were non-neutropenic, had improvement or resolution of clinical signs and symptoms, had a Candida isolate which was susceptible to fluconazole, and had documentation of 2 negative cultures drawn at least 24 hours apart. Patients were stratified by APACHE II score (20 or less or greater than 20) and by geographic region. Patients with Candida endocarditis were excluded from this analysis. Outcome was assessed by overall treatment success based on clinical (complete resolution or improvement in attributable signs and symptoms and radiographic abnormalities of the Candida infection and no additional antifungal therapy) and mycological (eradication or presumed eradication) response at the end of IV therapy. Deaths that occurred during IV study drug therapy were treated as failures.

In this study, 111/578 (19.2%) of the patients had baseline APACHE II scores of greater than 20, and 50/578 (8.7%) were neutropenic at baseline (absolute neutrophil count less than 500 cells/mm^3). Outcome, relapse and mortality data are shown for the recommended dose of MYCAMINE (100 mg/day) and caspofungin in Table 9.

Table 9. Efficacy Analysis: Treatment Success in Patients in Study 03-0-192 with Candidemia and Other Candida Infections
 | MYCAMINE 100 mg/day; n (%); % treatment difference; (95% CI) | Caspofungin 70/50 mg/day [70 mg loading dose on day 1 followed by 50 mg/day thereafter (caspofungin).]; n (%)
Treatment Success at End of IV Therapy [All patients who received at least one dose of study medication and had documented invasive candidiasis or candidemia. Patients with Candida endocarditis were excluded from the analyses.] | 135/191 (70.7); 7.4; (-2.0, 16.3) | 119/188 (63.3)
Success in Patients with Neutropenia at Baseline | 14/22 (63.6) | 5/11 (45.5)
Success by Site of Infection
Candidemia | 116/163 (71.2) | 103/161 (64)
Abscess | 4/5 (80) | 5/9 (55.6)
Acute Disseminated [A patient may have had greater than 1 organ of dissemination.] | 6/13 (46.2) | 5/9 (55.6)
Endophthalmitis | 1/3 | 1/1
Chorioretinitis | 0/3 | 0
Skin | 1/1 | 0
Kidney | 2/2 | 1/1
Pancreas | 1/1 | 0
Peritoneum | 1/1 | 0
Lung/Skin | 0/1 | 0
Lung/Spleen | 0/1 | 0
Liver | 0 | 0/2
Intraabdominal abscess | 0 | 3/5
Chronic Disseminated | 0/1 | 0
Peritonitis | 4/6 (66.7) | 2/5 (40)
Success by Organism [A patient may have had greater than 1 baseline infection species.]
C. albicans | 57/81 (70.4) | 45/73 (61.6)
C. glabrata | 16/23 (69.6) | 19/31 (61.3)
C. tropicalis | 17/27 (63) | 22/29 (75.9)
C. parapsilosis | 21/28 (75) | 22/39 (56.4)
C. krusei | 5/8 (62.5) | 2/3 (66.7)
C. guilliermondii | 1/2 | 0/1
C. lusitaniae | 2/3 (66.7) | 2/2
Relapse through 6 Weeks [All patients who had a culture-confirmed relapse or required systemic antifungal therapy in the post-treatment period for a suspected or proven Candida infection. Also includes patients who died or were not assessed in follow-up.]
Overall | 49/135 (36.3) | 44/119 (37)
Culture-confirmed relapse | 5 | 4
Required systemic antifungal therapy | 11 | 5
Died during follow-up | 17 | 16
Not assessed | 16 | 19
Overall study mortality | 58/200 (29) | 51/193 (26.4)
Mortality during IV therapy | 28/200 (14) | 27/193 (14)

In two cases of ophthalmic involvement assessed as failures in the above table due to missing evaluation at the end of IV treatment with MYCAMINE, therapeutic success was documented during protocol-defined oral fluconazole therapy.

14.2 Treatment of Esophageal Candidiasis in Adult and Pediatric Patients 4 Months of Age and Older

In two controlled trials involving 763 patients with esophageal candidiasis, 445 adults with endoscopically-proven candidiasis received MYCAMINE, and 318 received fluconazole for a median duration of 14 days (range 1 to 33 days).

MYCAMINE was evaluated in a randomized, double-blind study which compared MYCAMINE 150 mg/day (n = 260) to intravenous fluconazole 200 mg/day (n = 258) in adults with endoscopically-proven esophageal candidiasis. Most patients in this study had HIV infection, with CD4 cell counts less than 100 cells/mm^3. Outcome was assessed by endoscopy and by clinical response at the end of treatment. Endoscopic cure was defined as endoscopic grade 0, based on a scale of 0 to 3. Clinical cure was defined as complete resolution in clinical symptoms of esophageal candidiasis (dysphagia, odynophagia, and retrosternal pain). Overall therapeutic cure was defined as both clinical and endoscopic cure. Mycological eradication was determined by culture, and by histological or cytological evaluation of esophageal biopsy or brushings obtained endoscopically at the end of treatment. As shown in Table 10, endoscopic cure, clinical cure, overall therapeutic cure, and mycological eradication were comparable for patients in the MYCAMINE and fluconazole treatment groups.

Table 10. Endoscopic, Clinical, and Mycological Outcomes for Esophageal Candidiasis at End-of-Treatment
Treatment Outcome [Endoscopic and clinical outcome were measured in the modified intent-to-treat population, including all randomized patients who received 1 or more doses of study treatment. The mycological outcome was determined in the per protocol (evaluable) population, including patients with confirmed esophageal candidiasis who received at least 10 doses of study drug, and had no major protocol violations.] | MYCAMINE; 150 mg/day; n = 260 | Fluconazole; 200 mg/day; n = 258 | % Difference [Calculated as MYCAMINE – fluconazole.]; (95% CI)
Endoscopic Cure | 228 (87.7%) | 227 (88.0%) | -0.3% (-5.9, +5.3)
Clinical Cure | 239 (91.9%) | 237 (91.9%) | 0.06% (-4.6, +4.8)
Overall Therapeutic Cure | 223 (85.8%) | 220 (85.3%) | 0.5% (-5.6, +6.6)
Mycological Eradication | 141/189 (74.6%) | 149/192 (77.6%) | -3.0% (-11.6, +5.6)

Most patients (96%) in this study had C. albicans isolated at baseline. The efficacy of MYCAMINE was evaluated in less than 10 patients with Candida species other than C. albicans, most of which were isolated concurrently with C. albicans.

Relapse was assessed at 2 and 4 weeks post-treatment in patients with overall therapeutic cure at end of treatment. Relapse was defined as a recurrence of clinical symptoms or endoscopic lesions (endoscopic grade greater than 0). There was no statistically significant difference in relapse rates at either 2 weeks or through 4 weeks post-treatment for patients in the MYCAMINE and fluconazole treatment groups, as shown in Table 11.

Table 11. Relapse of Esophageal Candidiasis at Week 2 and through Week 4 Post-Treatment in Patients with Overall Therapeutic Cure at the End of Treatment
Relapse | MYCAMINE; 150 mg/day; n = 223 | Fluconazole; 200 mg/day; n = 220 | % Difference [Calculated as MYCAMINE – fluconazole; N = number of patients with overall therapeutic cure (both clinical and endoscopic cure at end-of-treatment);]; (95% CI)
Relapse [Relapse included patients who died or were lost to follow-up, and those who received systemic anti-fungal therapy in the post-treatment period.] at Week 2 | 40 (17.9%) | 30 (13.6%) | 4.3% (-2.5, 11.1)
Relapse through Week 4 (cumulative) | 73 (32.7%) | 62 (28.2%) | 4.6% (-4.0, 13.1)

In this study, 459 of 518 (88.6%) patients had oropharyngeal candidiasis in addition to esophageal candidiasis at baseline. At the end of treatment, 192/230 (83.5%) MYCAMINE-treated patients and 188/229 (82.1%) of fluconazole-treated patients experienced resolution of signs and symptoms of oropharyngeal candidiasis. Of these, 32.3% in the MYCAMINE group, and 18.1% in the fluconazole group (treatment difference = 14.2%; 95% confidence interval [5.6, 22.8]) had symptomatic relapse at 2 weeks post-treatment. Relapse included patients who died or were lost to follow-up, and those who received systemic antifungal therapy during the post-treatment period. Cumulative relapse at 4 weeks post-treatment was 52.1% in the MYCAMINE group and 39.4% in the fluconazole group (treatment difference 12.7%, 95% confidence interval [2.8, 22.7]).

14.3 Prophylaxis of Candida Infections in Hematopoietic Stem Cell Transplant Recipients

In a randomized, double-blind study, MYCAMINE (50 mg IV once daily) was compared to fluconazole (400 mg IV once daily) in 882 [adult (791) and pediatric (91)] patients undergoing an autologous or syngeneic (46%) or allogeneic (54%) stem cell transplant. All pediatric patients, except 2 per group, received allogeneic transplants. The status of the patients’ underlying malignancy at the time of randomization was: 365 (41%) patients with active disease, 326 (37%) patients in remission, and 195 (22%) patients in relapse. The more common baseline underlying diseases in the 476 allogeneic transplant recipients were: chronic myelogenous leukemia (22%), acute myelogenous leukemia (21%), acute lymphocytic leukemia (13%), and non-Hodgkin’s lymphoma (13%). In the 404 autologous and syngeneic transplant recipients the more common baseline underlying diseases were: multiple myeloma (37.1%), non-Hodgkin’s lymphoma (36.4%), and Hodgkin's disease (15.6%). During the study, 198 of 882 (22.4%) transplant recipients had proven graft-versus-host disease; and 475 of 882 (53.9%) recipients received immunosuppressive medications for treatment or prophylaxis of graft-versus-host disease.

Study drug was continued until the patient had neutrophil recovery to an absolute neutrophil count (ANC) of 500 cells/mm^3 or greater or up to a maximum of 42 days after transplant. The average duration of drug administration was 18 days (range 1 to 51 days). Duration of therapy was slightly longer in the pediatric patients who received MYCAMINE (median duration 22 days) compared to the adult patients who received MYCAMINE (median duration 18 days).

Successful prophylaxis was defined as the absence of a proven, probable, or suspected systemic fungal infection through the end of therapy (usually 18 days), and the absence of a proven or probable systemic fungal infection through the end of the 4-week post-therapy period. A suspected systemic fungal infection was diagnosed in patients with neutropenia (ANC less than 500 cells/mm^3); persistent or recurrent fever (while ANC less than 500 cells/mm^3) of no known etiology; and failure to respond to at least 96 hours of broad spectrum antibacterial therapy. A persistent fever was defined as four consecutive days of fever greater than 38ºC. A recurrent fever was defined as having at least one day with temperatures 38.5ºC or higher after having at least one prior temperature higher than 38ºC; or having two days of temperatures higher than 38ºC after having at least one prior temperature higher than 38ºC. Transplant recipients who died or were lost to follow-up during the study were considered failures of prophylactic therapy.

Successful prophylaxis was documented in 80.7% of adult and pediatric MYCAMINE recipients, and in 73.7% of adult and pediatric patients who received fluconazole (7.0% difference [95% CI = 1.5, 12.5]), as shown in Table 12, along with other study endpoints. The use of systemic antifungal therapy post-treatment was 42% in both groups.

The number of proven breakthrough Candida infections was 4 in the MYCAMINE and 2 in the fluconazole group.

The efficacy of MYCAMINE against infections caused by fungi other than Candida has not been established.

Table 12. Results from Clinical Study of Prophylaxis of Candida Infections in Hematopoietic Stem Cell Transplant Recipients
Outcome of Prophylaxis | MYCAMINE; 50 mg/day; (n = 425) | Fluconazole; 400 mg/day; (n = 457)
Success [Difference (MYCAMINE – fluconazole): +7.0% [95% CI=1.5, 12.5].] | 343 (80.7%) | 337 (73.7%)
Failure: | 82 (19.3%) | 120 (26.3%)
All Deaths [Through end-of-study (4 weeks post-therapy).]; Proven/probable fungal infection prior to death | 18 (4.2%); 1 (0.2%) | 26 (5.7%); 3 (0.7%)
Proven/probable fungal infection (not resulting in death) | 6 (1.4%) | 8 (1.8%)
Suspected fungal infection [Through end-of-therapy.] | 53 (12.5%) | 83 (18.2%)
Lost to follow-up | 5 (1.2%) | 3 (0.7%)

16 HOW SUPPLIED/STORAGE AND HANDLING

MYCAMINE is supplied as a sterile, white lyophilized powder for reconstitution for intravenous infusion, and is available in the following packaging configurations:

- cartons of 10 individually packaged 50 mg single-dose vials, coated with a light protective film and sealed with a blue flip-off cap. (NDC 0469-3250-10)
- cartons of 10 individually packaged 100 mg single-dose vials, coated with a light protective film and sealed with a red flip-off cap. (NDC 0469-3211-10)

Storage

Unopened vials of lyophilized material must be stored at room temperature, 25°C (77°F); excursions permitted to 15°C to 30°C (59°F to 86°F) [see USP Controlled Room Temperature].

Store the reconstituted product at 25°C (77°F) [see Dosage and Administration (2.4)]

Store the diluted solution at 25°C (77°F) [see Dosage and Administration (2.4)]

Protect from light.

17 PATIENT COUNSELING INFORMATION

Hypersensitivity

Inform patients about the serious adverse effects of MYCAMINE including hypersensitivity reactions
e.g., anaphylaxis and anaphylactoid reactions including shock.

Hepatic

Inform patients about the serious adverse effects of MYCAMINE including hepatic effects e.g., abnormal liver tests, hepatic impairment, hepatitis or worsening hepatic failure.

Hematologic

Inform patients about the serious adverse effects of MYCAMINE including hematological effects e.g., acute intravascular hemolysis, hemolytic anemia and hemoglobinuria.

Renal

Inform patients about the serious adverse effects of MYCAMINE including renal effects e.g., elevations in BUN and creatinine, renal impairment or acute renal failure.

Embryo-Fetal Toxicity

Advise pregnant women and females of reproductive potential of the potential risk of MYCAMINE to a fetus. Advise females to inform their healthcare provider of a known or suspected pregnancy.

Concomitant Medications

Instruct patients to inform their healthcare provider of any other medications they are currently taking with MYCAMINE, including over-the-counter medications.

Manufactured by:
Astellas Pharma Tech Co., Ltd. Takaoka Plant
30 Toidesakae-machi, Takaoka city, Toyama 939-1118, Japan

Marketed by:
Astellas Pharma US, Inc.
Northbrook, IL 60062 USA

MYCAMINE® is a registered trademark of Astellas Pharma Inc.

286316-MYC

PRINCIPAL DISPLAY PANEL – 50 mg/vial

NDC 0469-3250-10

Mycamine®
(micafungin) for injection

50 mg/vial

For Intravenous Infusion Only
Single-Dose Vial
Discard unused portion

astellas 325010

PRINCIPAL DISPLAY PANEL – 100 mg/vial

NDC 0469-3211-10

Mycamine®
(micafungin) for injection

100 mg/vial

For Intravenous Infusion Only
Single-Dose Vial
Discard unused portion

astellas 321110